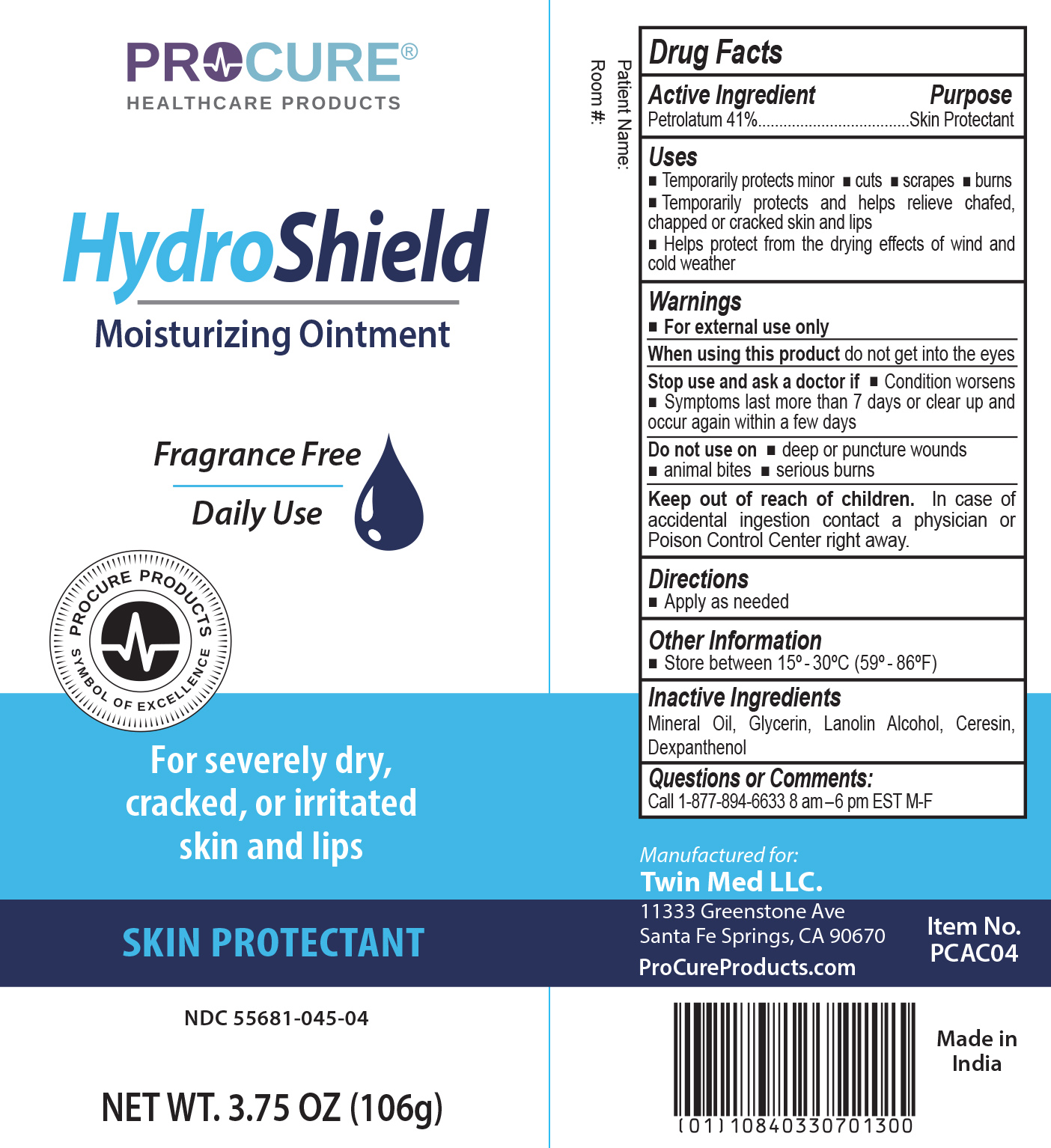 DRUG LABEL: ProCure HydroShield
NDC: 55681-045 | Form: OINTMENT
Manufacturer: Twin Med LLC
Category: otc | Type: HUMAN OTC DRUG LABEL
Date: 20251201

ACTIVE INGREDIENTS: PETROLATUM 41 g/100 g
INACTIVE INGREDIENTS: LANOLIN ALCOHOLS; GLYCERIN; CERESIN; DEXPANTHENOL; MINERAL OIL

Active Ingredient

Active Ingredient:Petrolatum 41%

Purpose

Purpose: Skin Protectant

Uses

- Temporarily protects minor: cuts, scrapes, burns
- Temporarily protects and helps relieve chafed, chapped or cracked skin and lips
- Helps protect from the drying effects of wind and cold weather

Warnings

For external use only

When using this product

When using this productdo not get into the eyes

Stop use and ask a doctor if

- Condition worsens
- Symptoms last more than 7 days or clear up and occur again within a few days

Do not use on deep or puncture wounds, animal bites, serious burns

Keep out of reach of children.In case of accidental ingestion contact a physician or Poison Control Center right away

Directions

Directions:Apply as needed

Inactive Ingredients

Mineral Oil, Glycerin, Lanolin Alcohol, Ceresin, Dexpanthenol